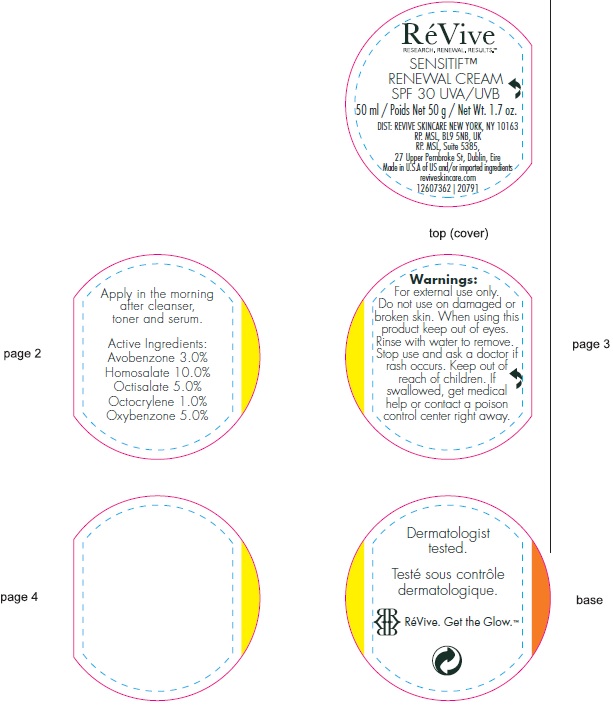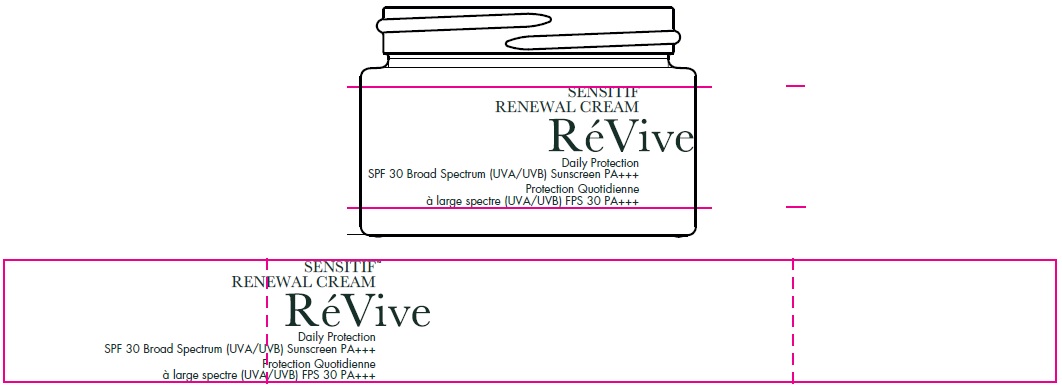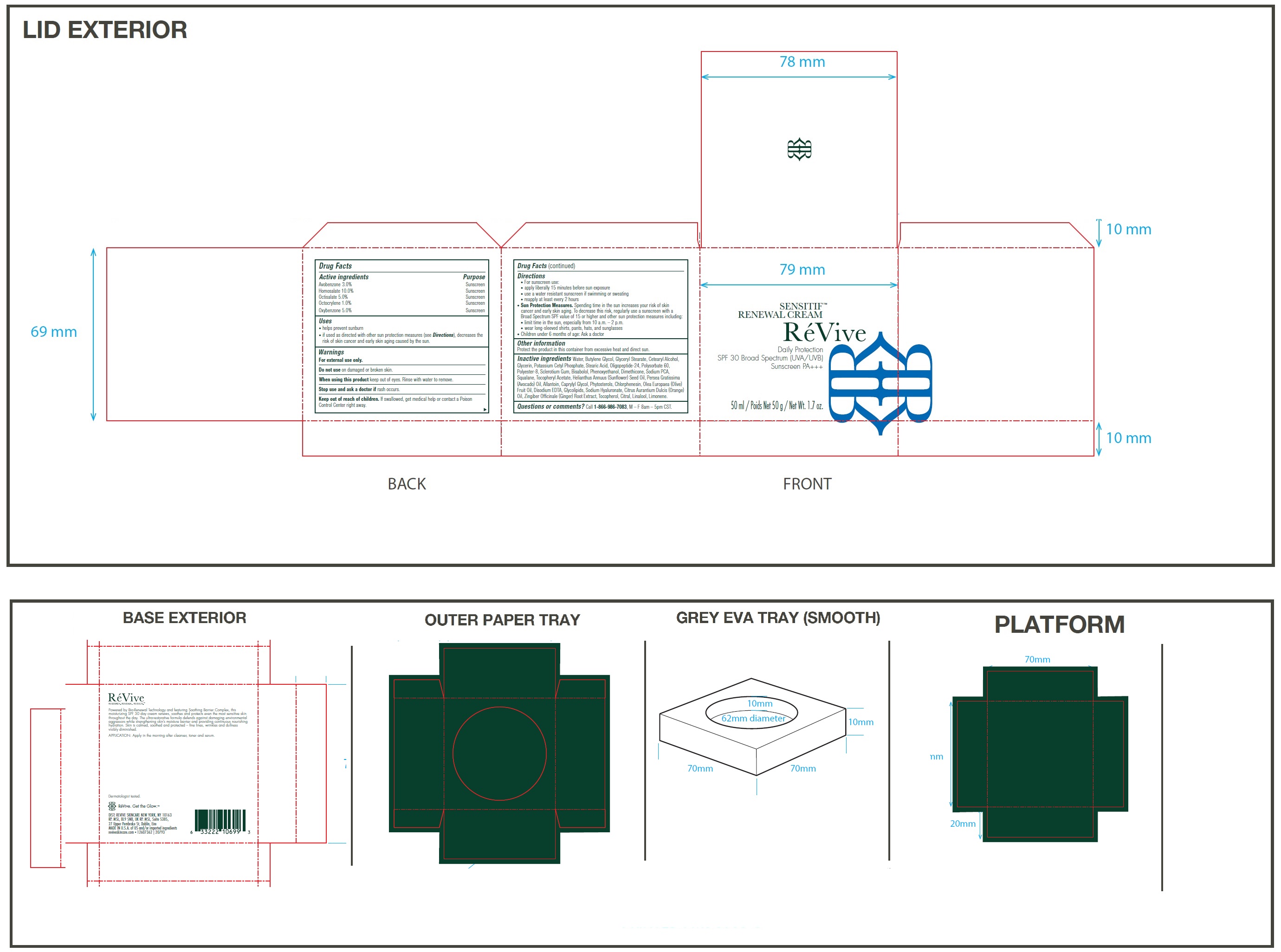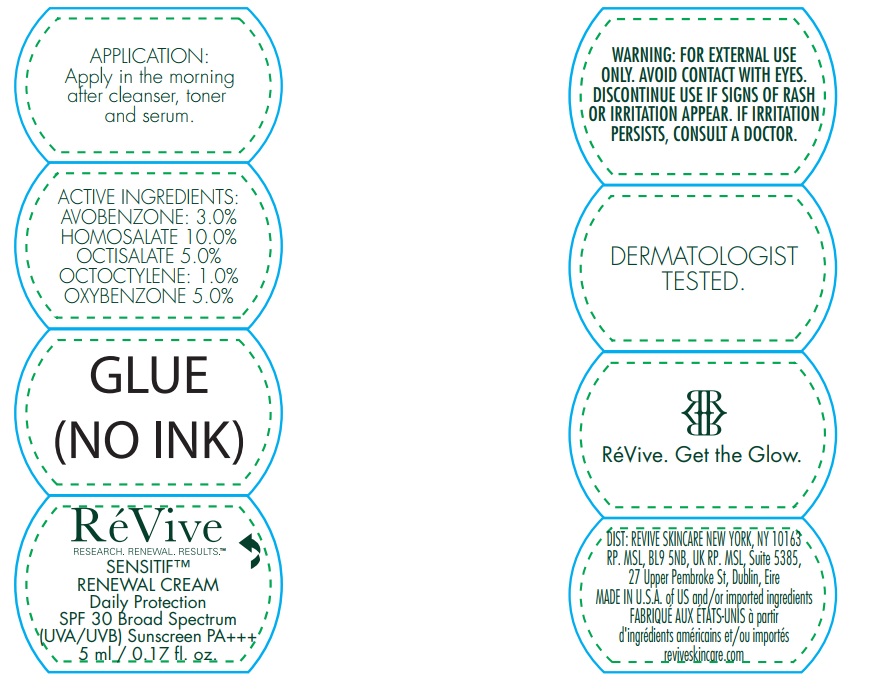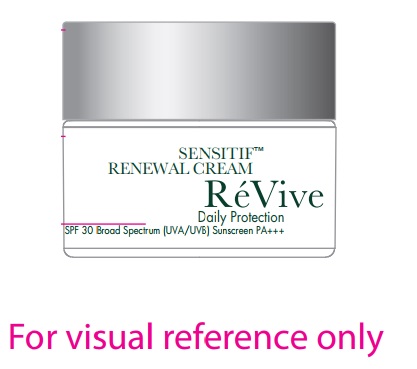 DRUG LABEL: Sensitif Renewal Cream Daily Protection SPF 30 Broad Spectrum UVA UVB Sunscreen
NDC: 82691-035 | Form: CREAM
Manufacturer: RV Skincare LLC
Category: otc | Type: HUMAN OTC DRUG LABEL
Date: 20260120

ACTIVE INGREDIENTS: AVOBENZONE 30 mg/1 mL; HOMOSALATE 100 mg/1 mL; OCTISALATE 50 mg/1 mL; OCTOCRYLENE 10 mg/1 mL; OXYBENZONE 50 mg/1 mL
INACTIVE INGREDIENTS: WATER; BUTYLENE GLYCOL; GLYCERYL MONOSTEARATE; CETOSTEARYL ALCOHOL; GLYCERIN; POTASSIUM CETYL PHOSPHATE; STEARIC ACID; POLYSORBATE 60; BETASIZOFIRAN; LEVOMENOL; PHENOXYETHANOL; DIMETHICONE; SODIUM PYRROLIDONE CARBOXYLATE; SQUALANE; .ALPHA.-TOCOPHEROL ACETATE; SUNFLOWER OIL; AVOCADO OIL; ALLANTOIN; CAPRYLYL GLYCOL; CHLORPHENESIN; OLIVE OIL; EDETATE DISODIUM ANHYDROUS; HYALURONATE SODIUM; ORANGE OIL, COLD PRESSED; GINGER; TOCOPHEROL; CITRAL; LINALOOL, (+/-)-; LIMONENE, (+)-

Sensitif Renewal Cream Daily Protection SPF 30 Broad Spectrum (UVA/UVB) Sunscreen

Active ingredients

Avobenzone 3.0% Homosalate 10.0% Octisalate 5.0% Octocrylene 1.0% Oxybenzone 5.0%

Purpose

Sunscreen

Uses

- helps prevent sunburn
- if used as directed with other sun protection measures (see), decreases the risk of skin cancer and early skin aging caused by the sun. Directions

Warnings

For external use only.

Do not use

on damaged or broken skin.

When using this product

keep out of eyes. Rinse with water to remove.

Stop use and ask a doctor if

rash occurs.

Keep out of reach of children.

If swallowed, get medical help or contact a Poison Control Center right away.

Directions

- For sunscreen use:
- apply liberally 15 minutes before sun exposure
- use a water resistant sunscreen if swimming or sweating
- reapply at least every 2 hours
- Spending time in the sun increases your risk of skin cancer and early skin aging. To decrease this risk, regularly use a sunscreen with a Broad Spectrum SPF value of 15 or higher and other sun protection measures including: Sun Protection Measures.
- limit time in the sun, especially from 10 a.m. - 2 p.m.
- wear long-sleeved shirts, pants, hats, and sunglasses
- Children under 6 months of age: Ask a doctor

Other information

Protect the product in this container from excessive heat and direct sun.

Inactive ingredients

Water, Butylene Glycol, Glyceryl Stearate, Cetearyl Alcohol, Glycerin, Potassium Cetyl Phosphate, Stearic Acid, Oligopeptide-24, Polysorbate 60, Polyester-8, Sclerotium Gum, Bisabolol, Phenoxyethanol, Dimethicone, Sodium PCA, Squalane, Tocopheryl Acetate, Helianthus Annuus (Sunflower) Seed Oil, Persea Gratissima (Avocado) Oil, Allantoin, Caprylyl Glycol, Phytosterols, Chlorphenesin, Olea Europaea (Olive) Fruit Oil, Disodium EDTA, Glycolipids, Sodium Hyaluronate, Citrus Aurantium Dulcis (Orange) Oil, Zingiber Officinale (Ginger) Root Extract, Tocopherol, Citral, Linalool, Limonene.

Questions or comments?

Call , M – F 8am – 5pm CST. 1-866-986-7083